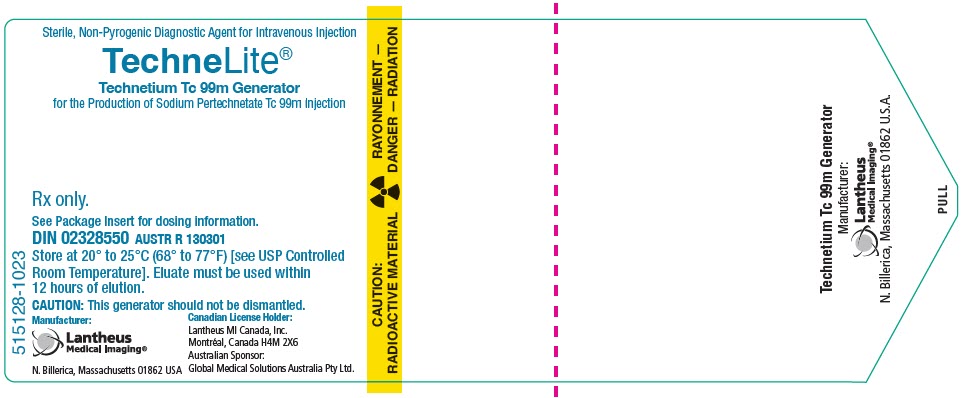 DRUG LABEL: TechneLite
NDC: 11994-090 | Form: INJECTION, SOLUTION
Manufacturer: Lantheus Medical Imaging, Inc.
Category: prescription | Type: HUMAN PRESCRIPTION DRUG LABEL
Date: 20241101

ACTIVE INGREDIENTS: TECHNETIUM TC-99M SODIUM PERTECHNETATE 250 mCi/1 mL

TechneLite®
Technetium Tc 99m Generator

FOR DIAGNOSTIC USE

For the Production of Sodium Pertechnetate Tc 99m Injection

DESCRIPTION

DESCRIPTION: Sodium Pertechnetate Tc 99m Injection, as eluted according to the elution instructions with Lantheus Medical Imaging, Inc. TECHNELITE®, Technetium Tc 99m Generator, is in 0.9% Sodium Chloride Injection, USP as a sterile, non-pyrogenic, diagnostic radiopharmaceutical suitable for intravenous injection and direct instillation. The pH is 4.5-7.5. The eluate should be clear, colorless, and free from visible foreign material. Each eluate of the TECHNELITE®, Technetium Tc 99m Generator should not contain more than 0.0056MBq (0.15 microcuries) of Molybdenum Mo99 per 37MBq (1 millicurie) of Technetium Tc 99m per administered dose at the time of administration, and not more than 10 micrograms of aluminum per milliliter of the Technetium Tc 99m Generator eluate, both of which must be determined by the user before administration. Since the eluate does not contain an antimicrobial agent, it should not be used later than one (1) working day after the elution (12 hours).

Lantheus Medical Imaging, Inc. TECHNELITE®, Technetium Tc 99m Generator consists of a column containing uranium fission produced Molybdenum Mo99 adsorbed on alumina. The terminally sterilized and sealed column is enclosed in a lead shield; the shield and other components are sealed in a cylindrical plastic container with an attached handle. Built into the top surface are two recessed wells marked SALINE CHARGE and COLLECT. Needles protruding from these two wells accommodate supplied sterile eluant charge vials and sterile eluate collection vials. The eluting solvent consists of 0.9% Sodium Chloride Injection, USP, prepacked into septum-sealed vials, to make the solution isotonic.

The eluate collection vial is evacuated, sterile and non-pyrogenic. A sterile 0.22 micrometer bacteriological filter is incorporated between the column outlet and the collection vials. During and subsequent to elution, the eluate collection vial should be kept in a radiation shield. The Generator is shipped with a silicone needle seal over the charge needle and a vented needle cover over the collect needle. A sterile collect needle seal is supplied for the customer to aseptically reseal the collect needle after each elution.

Physical Characteristics

Technetium Tc 99m decays by isomeric transition with a physical half-life of 6.02 hours.^1 Photons that are useful for imaging studies are listed in Table 1.

Table 1. Principal Radiation Emission Data - Technetium Tc 99m
Radiation | Mean %/Disintegration | Mean Energy (keV)
Gamma-2 | 89.07 | 140.5

External Radiation

The specific gamma ray constant for Technetium Tc 99m is 5.4 microcoulombs/Kg-MBq-hr (0.795 R/mCi-hr) at 1cm. The first half-value thickness is 0.023cm of lead (Pb). To facilitate control of radiation exposure from millicurie amounts of Technetium Tc 99m, for example, the use of a 0.27 cm thick standard radiation elution lead shield will attenuate the radiation emitted by a factor of about 1000. A range of values for the relative attenuation of the radiation emitted by this radionuclide that results from interposition of various thicknesses of lead is shown in Table 2.

NOTE: Because the generator is well contained and essentially dry, there is little likelihood of contamination due to damage in transit.

Table 2. Radiation Attenuation of Technetium Tc 99m by Lead Shielding
Shield Thickness lead (Pb) cm | Coefficient of Attenuation
0.023 | 0.5
0.09 | 10^-1
0.18 | 10^-2
0.27 | 10^-3
0.33 | 10^-4

Molybdenum Mo99 decays to Technetium Tc 99m with a Molybdenum Mo99 half-life of 66 hours. This means that only 78% of the activity remains after 24 hours; 60% remains after 48 hours, etc. (see Table 3). All units have a minimum of 38 mm, 1.5 inches (~ 6 half-value layers) of lead surrounding the activity. (See Table 3.)

Table 3. Molybdenum Mo99 Decay Chart Half-Life 66.0 Hours
Days | Percent Remaining | Days | Percent Remaining
0 | 100 | 10 | 8
1 | 78 | 11 | 6
2 | 60 | 12 | 5
3 | 47 | 13 | 4
4 | 37 | 14 | 3
5 | 28 | 15 | 2
6 | 22 | 20 | 0.6
7 | 17 | 25 | 0.2
8 | 13 | 30 | 0.05
9 | 10

The physical decay characteristics of Molybdenum Mo99 are such that approximately 88% of the decaying Molybdenum Mo99 atoms form Technetium Tc 99m. Since the Molybdenum Mo99 is constantly decaying to fresh Technetium Tc 99m, it is possible to elute the generator at any time. However, the total amount of Technetium Tc 99m available will depend on the time interval from the previous elution, the quantity of Molydenum Mo99 remaining and the efficiency of the elution. Approximately 47% of maximum Technetium Tc 99m is reached after 6 hours and 95% after 23 hours.

The elution vial shield has a wall thickness of 7.9 mm, 0.31 inches, and reduces transmitted Technetium Tc 99m radiation essentially to zero. To correct for physical decay of Tc 99m, the fractions that remain at selected intervals of time are shown in Table 4.

Table 4. Physical Decay Chart: Technetium Tc 99m Half-Life 6 Hours
Hours | Percent Remaining | Hours | Percent Remaining
0* | 100.0 | 9 | 35
1 | 89 | 10 | 32
2 | 79 | 11 | 28
3 | 71 | 12 | 25
4 | 63 | 14 | 20
5 | 56 | 16 | 16
6 | 50 | 18 | 13
7 | 45 | 24 | 6
8 | 40
*Calibration Time

CLINICAL PHARMACOLOGY

CLINICAL PHARMACOLOGY: The pertechnetate ion distributes in the body similarly to the iodide ion but is not organified when trapped in the thyroid gland. It also concentrates in the choroid plexus, thyroid gland, salivary glands, and stomach. However, in contrast to the iodide ion, the pertechnetate ion is released unchanged from the thyroid gland.

After intravascular administration the pertechnetate ion gradually equilibrates with the extracellular space. A fraction is promptly excreted via the kidneys.

Following the administration of Sodium Pertechnetate Tc 99m Injection as an eye drop, the drug mixes with tears within the conjunctival space. Within seconds to minutes it leaves the conjunctival space and escapes into the inferior meatus of the nose through the nasolacrimal drainage system. During this process the pertechnetate ion passes through the canaliculi, the lacrimal sac and the nasolacrimal duct. In the event of any anatomical or functional blockage of the drainage system there will be a backflow resulting in tearing (epiphora). Thus the pertechnetate escapes the conjunctival space in the tears.

While the major part of the pertechnetate escapes within a few minutes of normal drainage and tearing, it has been documented that there is some degree of transconjunctival absorption with a fractional turnover rate of 0.015/min in normal individuals, 0.021/min in patients without any sac and 0.027/min in patients with inflamed conjunctiva due to chronic dacryocystitis. Individual values may vary but these rates are probably representative and indicate that the maximum possible pertechnetate absorbed will remain below one thousandth of that used in other routine diagnostic procedures.

INDICATIONS AND USAGE:

The Technelite generator is a source of sodium pertechnetate Tc 99m for use in the preparation of FDA-approved diagnostic radiopharmaceuticals, as described in the labeling of these diagnostic radiopharmaceutical kits.

Sodium Pertechnetate Tc 99m Injection is used IN ADULTS as an agent for:

Thyroid Imaging
Salivary Gland Imaging
Urinary Bladder Imaging (direct isotopic cystography) for the detection of vesico-ureteral reflux.
Nasolacrimal Drainage System Imaging

Sodium Pertechnetate Tc 99m Injection is used IN CHILDREN as an agent for:

Thyroid Imaging
Urinary Bladder Imaging (direct isotopic cystography) for the detection of vesico-ureteral reflux.

CONTRAINDICATIONS: None known.

WARNINGS

WARNINGS: Radiation risks associated with the use of Sodium Pertechnetate Tc 99m Injection are greater in children than in adults and, in general, the younger the child, the greater the risk owing to greater absorbed radiation doses and longer life-expectancy. These greater risks should be taken firmly into account in all benefit-risk assessments involving children.

Long-term cumulative radiation exposure may be associated with an increased risk of cancer.

PRECAUTIONS:

General

As in the use of any radioactive material, care should be taken to minimize radiation exposure to the patient consistent with proper patient management and to ensure minimum radiation exposure to occupational workers.

Since the eluate does not contain an antimicrobial agent, it should not be used after 12 hours from the time of TECHNELITE®, Technetium Tc 99m Generator elution.

After the termination of the nasolacrimal imaging procedure, blowing the nose and washing the eyes with sterile distilled water or an isotonic sodium chloride solution will further minimize the radiation dose.

Radiopharmaceuticals should be used only by physicians who are qualified by training and experience in the safe handling of radionuclides and whose experience and training have been approved by the appropriate government agency authorized to license the use of radionuclides.

Carcinogenesis, Mutagenesis, Impairment of Fertility

No animal studies have been performed to evaluate carcinogenic potential or whether Sodium Pertechnetate Tc 99m affects fertility in males or females.

Pregnancy

Animal reproductive studies have not been conducted with Sodium Pertechnetate Tc 99m. It is also not known whether Sodium Pertechnetate Tc 99m can cause fetal harm when administered to a pregnant woman or can affect reproduction capacity. Sodium Pertechnetate Tc 99m Injection should be given to a pregnant woman only if clearly needed.

Ideally examinations using radiopharmaceuticals, especially those elective in nature, of a woman of childbearing capability should be performed during the first few (approximately 10) days following the onset of menses.

Nursing Mothers

Sodium Pertechnetate Tc 99m is excreted in human milk during lactation; therefore formula feedings should be substituted for breast feeding.

This radiopharmaceutical preparation should not be administered to pregnant or lactating women unless expected benefits to be gained outweigh the potential risks.

Pediatric Use

See INDICATIONS and DOSAGE AND ADMINISTRATION sections. Also see the description of additional risks under WARNINGS.

Geriatric Use

Clinical studies of TechneLite® did not include sufficient numbers of subjects aged 65 and over to determine whether they respond differently from younger subjects. Other reported clinical experience has not identified differences in responses between the elderly and younger patients. In general, dose selection for an elderly patient should be cautious, usually starting at the low end of the dosing range, reflecting the greater frequency of decreased hepatic, renal, or cardiac function, and of concomitant disease or other drug therapy.

ADVERSE REACTIONS

ADVERSE REACTIONS: Allergic reactions including anaphylaxis have been reported infrequently following the administration of Sodium Pertechnetate Tc 99m Injection.

DOSAGE AND ADMINISTRATION: Sodium Pertechnetate Tc 99m Injection is usually administered by intravascular injection. For imaging the urinary bladder and ureters (direct isotopic cystography), the Sodium Pertechnetate Tc 99m Injection is administered by direct instillation aseptically into the bladder via a urethral catheter, following which the catheter is flushed with approximately 200 mL of 0.9% Sodium Chloride Injection, USP directly into the bladder. The dosage employed varies with each diagnostic procedure. When imaging the nasolacrimal drainage system, instill the Sodium Pertechnetate Tc 99m Injection by the use of a device such as a micropipette or similar method which will ensure the accuracy of the dose.

The suggested dose range employed for various diagnostic indications in the average ADULT PATIENT (70kg) is:

Vesico-ureteral Imaging | 18.5 to 37MBq (0.5 to 1mCi)
Thyroid Gland Imaging | 37 to 370MBq (1 to 10mCi)
Salivary Gland Imaging | 37 to 185MBq (1 to 5mCi)
Nasolacrimal Drainage System | Maximum 3.7MBq (100µCi)

The recommended dosage range in PEDIATRIC PATIENTS is:

Vesico-ureteral Imaging | 18.5 to 37MBq (0.5 to 1mCi)
Thyroid Gland Imaging | 2.22 to 2.96MBq (60 to 80µCi)/kg body weight

The patient dose should be measured by a suitable radioactivity calibration system immediately prior to administration of the dose.

Parenteral drug products should be inspected visually for particulate matter and discoloration prior to administration whenever solution and container permit. The solution to be administered as the patient dose should be clear and contain no particulate matter. Do not use an eluate of the TECHNELITE®, Technetium Tc 99m Generator later than one (1) working day after elution (12 hours).

Radiation Dosimetry

The estimated absorbed radiation doses to an average ADULT and Pediatric patient from an intravenous injection of a maximum dose of 1110MBq (30 millicuries) of Sodium Pertechnetate Tc 99m Injection distributed uniformly in the total body are shown in Tables 5 and 6.

Table 5. Adult Absorbed Radiation Doses (mGy) from Intravenous Injection
Organ | Absorbed Radiation Dose (mGy) for a 1110 MBq (30mCi) dose
Adrenals | 4.1
Urinary Bladder Wall | 20
Bone Surfaces | 6.2
Brain | 2.2
Breasts | 2
Gallbladder Wall | 8.3
Stomach Wall | 29
Small Intestine | 18
ULI Wall | 63
LLI Wall | 23
Heart Wall | 3.5
Kidneys | 6
Liver | 4.7
Lungs | 2.9
Muscle | 3.6
Ovaries | 11
Pancreas | 6.3
Red Marrow | 4.1
Skin | 2
Spleen | 4.8
Testes | 3.1
Thymus | 2.7
Thyroid | 24
Uterus | 9
Remaining Tissues | 3.9
Effective Dose (mSv) | 14
To obtain radiation absorbed dose in rads (30 mCi dose) from the above table, divide individual organ values by a factor of 10 (does not apply for effective dose).

Table 6. Pediatric Absorbed Radiation Doses (mGy) from Intravenous Injection
Age | 15 years | 10 years | 5 years | 1 year
Administered activity in MBq (mCi) | 1110 (30) | 740 (20) | 555 (15) | 370 (10)
Organ
Adrenals | 5.3 | 5.4 | 6.2 | 7.1
Urinary Bladder Wall | 26 | 22 | 18 | 22
Bone Surfaces | 7.6 | 7.5 | 8.1 | 10
Brain | 2.8 | 3.1 | 3.7 | 4.5
Breasts | 2.6 | 2.6 | 3.2 | 4.1
Gallbladder Wall | 11 | 12 | 13 | 13
Stomach Wall | 38 | 36 | 43 | 59
Small Intestine | 22 | 23 | 26 | 30
ULI Wall | 81 | 89 | 110 | 140
LLI Wall | 31 | 33 | 40 | 48
Heart Wall | 4.5 | 4.6 | 5.2 | 6.4
Kidneys | 7.2 | 6.9 | 7.8 | 8.5
Liver | 6 | 6.7 | 8 | 9.1
Lungs | 3.8 | 3.8 | 4.4 | 5.3
Muscle | 4.5 | 4.5 | 5 | 6
Ovaries | 14 | 13 | 14 | 17
Pancreas | 8.1 | 8.2 | 8.9 | 10
Red Marrow | 5.1 | 5 | 5.2 | 6
Skin | 2.5 | 2.6 | 3.2 | 3.8
Spleen | 6 | 6 | 6.7 | 7.8
Testes | 4.1 | 4.3 | 4.9 | 6
Thymus | 3.6 | 3.5 | 4.2 | 5.3
Thyroid | 40 | 41 | 67 | 81
Uterus | 11 | 11 | 12 | 14
Remaining Tissues | 4.8 | 4.8 | 5.4 | 6.4
Effective Dose (mSv) | 19 | 19 | 23 | 29
To obtain radiation absorbed dose in rads (30 mCi dose) from the above table, divide individual organ values by a factor of 10 (does not apply for effective dose).

The estimated absorbed radiation doses to an average ADULT from the instillation of Sodium Pertechnetate Tc 99m Injection for imaging the nasolacrimal drainage system are shown in Table 7.

Table 7. Absorbed Radiation Dose from Dacryoscintigraphy Using Sodium Pertechnetate Tc 99m
 | Absorbed Dose
Target Organ | mGy/ 3.7MBq | (rad/ 100µCi)
Eye Lens: If lacrimal fluid turnover is 16%/min If lacrimal fluid turnover is 100%/min If drainage system is blocked Total Body* Ovaries* Testes* Thyroid* | 0.140 0.022 4.020 0.011 0.030 0.009 0.130 | 0.014 0.002 0.402 0.001 0.003 0.001 0.013
* Assuming no blockage of drainage system

In pediatric patients, an average 30 minute exposure to 37MBq (1 millicurie) of Sodium Pertechnetate Tc 99m Injection following instillation for direct cystography, results in an estimated absorbed radiation dose shown in Table 8.

Table 8. Pediatric Absorbed Radiation Dose from Cystography
Age | Bladder wall dose, mGy (rad) | Gonadal dose, mGy (rad)
1 year | 3.6 (0.36) | 0.15 (0.015)
5 years | 2.0 (0.2) | 0.095 (0.0095)
10 years | 1.3 (0.13) | 0.066 (0.0066)
15 years | 0.92 (0.092) | 0.046 (0.0046)

HOW SUPPLIED

HOW SUPPLIED: Lantheus Medical Imaging TechneLite®, (Technetium Tc 99m Generator) for the Production of Sodium Pertechnetate Tc 99m Injection is supplied in a multi-dose container and is available in the following quantities of radioactivity of Mo99 on the calibration date (date of manufacture) as specified on the product lot identification label affixed to the generator:

Table 9 Available Quantities of Radioactivity
High Enriched Uranium (HEU) |  |  |  | Low Enriched Uranium (LEU)
NDC # | GBq of Mo99 | Ci of Mo99 |  | NDC # | GBq of Mo99 | Ci of Mo99
11994-090-36 | 37.0 | 1 |  | 11994-091-36 | 37.0 | 1
11994-090-73 | 74.0 | 2 |  | 11994-091-73 | 74.0 | 2
11994-090-92 | 92.5 | 2.5 |  | 11994-091-92 | 92.5 | 2.5
11994-090-01 | 111.0 | 3 |  | 11994-091-01 | 111.0 | 3
11994-090-03 | 148.0 | 4 |  | 11994-091-03 | 148.0 | 4
11994-090-04 | 166.5 | 4.5 |  | 11994-091-04 | 166.5 | 4.5
11994-090-05 | 185.0 | 5 |  | 11994-091-05 | 185.0 | 5
11994-090-06 | 222.0 | 6 |  | 11994-091-06 | 222.0 | 6
11994-090-07 | 277.5 | 7.5 |  | 11994-091-07 | 277.5 | 7.5
11994-090-09 | 370.0 | 10 |  | 11994-091-09 | 370.0 | 10
11994-090-10 | 462.5 | 12.5 |  | 11994-091-10 | 462.5 | 12.5
11994-090-11 | 555.0 | 15 |  | 11994-091-11 | 555.0 | 15
11994-090-12 | 666.0 | 18 |  | 11994-091-12 | 666.0 | 18
11994-090-13 | 740.0 | 20 |  | 11994-091-13 | 740.0 | 20

Each generator is supplied with the following standard components:

Collect Needle Seal
Eluant Charge Vials (may be supplied separately)
Eluate Collection Vials (may be supplied separately)
1 Package Insert
6 Radiation Labels (Collection Vial)
6 Radiation Labels (Eluting Shield)

First order generators are shipped with the following accessory components:

2 Eluting Shields

Additional quantities of these components may be obtained at the customer's request.

STORAGE AND HANDLING

STORAGE: Store generator and Sodium Pertechnetate Tc 99m Injection at 20° to 25°C (68° to 77°F) [see USP Controlled Room Temperature].

EXPIRATION: The expiration time of the Sodium Pertechnetate Tc 99m solution is not later than 12 hours after elution. If the eluate is to be used to reconstitute a kit for the preparation of a Technetium Tc 99m radiopharmaceutical, the kit should not be used after 12 hours from time of Generator elution or after the expiration time stated on the labeling for the prepared drug, whichever is earlier.

The generator should not be used after the expiration date stated on the label.

ELUTION INSTRUCTIONS - TOTAL ELUTION METHOD

1. Waterproof gloves should be worn during elution.
2. Remove dust (clear plastic) cover of generator.
3. Perform all subsequent operations aseptically.
4. Remove silicone needle seal from eluant charge well. Discard as radioactive waste.
5. Remove flip-off seal and swab septum of eluant charge vial with a bactericide (such as 70% isopropyl alcohol), allow to dry, and insert the vial into charge well. Vial should be firmly inserted to assure puncture of septum. Caution: Excessive use of bactericides containing alcohol may adversely affect Technetium Tc 99m yield.
6. Open elution shield base and insert an eluate collection vial from which the flip-off seal has been removed. Screw base back on securely. Swab the exposed vial septum with a bactericide and allow to dry.
7. Remove vented needle cover from collect well. Discard as radioactive waste.
8. Insert shielded eluate collection vial in collect well. Elution should commence within 30 seconds and can be visually checked by the appearance of bubbles in the eluant charge vial. To assure proper yield and functioning, elution must proceed to completion as evidenced by emptying of the charge vial. Allow generator to elute for at least 3 minutes after the charge has been drained, or for a total of 6 minutes.
  ****NOTE 1 (non-eluting generator): If bubbles do not appear in the eluant charge vial within 30 seconds, remove the eluate collection vial to prevent vacuum loss; then remove and reinsert the charge vial. Reinsert the eluate collection vial and if elution does not commence, use a second shielded collection vial. If the elution still does not commence, contact Lanthues Medical Imaging, Inc.
  ****NOTE 2 (partial eluting generator): If the saline charge vial does not fully empty or the expected eluate volume is not recovered, remove the evacuated collection vial and the saline charge vial. Insert a new saline charge vial and a new evacuated collection vial. Allow the elution process to complete. If the replacement saline charge vial does not fully empty or the expected eluate volume is not recovered in the replacement collection vial, contact Lantheus Medical Imaging, Inc. DO NOT USE ELUATE COLLECTED FROM A PARTIALLY ELUTED GENERATOR.
  Caution: Tampering with the internal components could compromise sterility and present a radiation hazard. This generator should not be dismantled.
9. After elution has been completed, remove shield containing the collection vial. Obtain the collect needle seal, and using a bactericide, swab the insertion end of the collect needle seal and insert over the collect needle. The eluant vial is sterile and should stay in place until the next elution, functioning as a seal for the needles within the charge well. Upon initiating the next elution, discard the empty eluant vial as radioactive waste and retain the collect needle seal for subsequent elutions.
10. Perform the Assay and Radiometric Molybdenum Test Procedures described below for each elution performed.
11. Fill out and attach the appropriate supplied pressure sensitive radioactivity labels to the elution shield containing the filled eluate collection vial. Do not use an eluate of the Technetium Tc 99m Generator later than 1 working day after the time of elution (12 hours).
12. Use a shielded syringe when introducing the Sodium Pertechnetate Tc 99m solution into mixing vials.
13. Maintain adequate shielding during the life of the radioactive preparation by using a lead vial shield and cover, and use a shielded syringe for withdrawing and injecting the preparation.

ASSAY INSTRUCTIONS FOR THE TECHNELITE®, TECHNETIUM Tc 99m GENERATOR ELUATE

The TECHNELITE®, Technetium Tc 99m Generator Eluate may be assayed using an ionization chamber dose calibrator. The manufacturer's instructions for operation of the dose calibrator should be followed for measurement of Technetium Tc 99m and Molybdenum Mo99 activity in the generator eluate. The Molybdenum 99/Technetium 99m ratio is to be determined at the time of each elution prior to administration, and from that ratio, the expiration time (up to 12 hours) of the eluate mathematically determined. Each eluate must meet or exceed the purity requirements of the current United States Pharmacopeia; that is, not more than 0.0056MBq (0.15 microcurie) of Molybdenum 99 per 37MBq (1 millicurie) of Technetium 99m per administered dose at the time of administration.

RADIOMETRIC MOLYBDENUM TEST PROCEDURE

This method is based on the fact that most Technetium Tc 99m radiation can be readily shielded and only the more energetic gamma rays from Molybdenum Mo99 (739KeV and 778KeV) are counted in the 550-850KeV energy range. The entire eluate may be assayed for Molybdenum Mo99 activity as follows:

1. A Cesium Cs 137 reference source which has the same geometry as the generator eluate must be used to standardize the well counter.
2. Determine the background after setting the window to the 550-850KeV energy range.
3. Count the Technetium Tc 99m eluate in its lead shield (thereby shielding out Technetium Tc 99m) by placing over the well or probe.
4. Count the Cs 137 reference source in the same shield geometry for the same time period.
5. Compute Molybdenum Mo99 activity in the eluate as follows:
  µCi Molybdenum = µCi simulated Mo99 x net cpm Eluate
  Mo99 (total) net cpm simulated Mo99 reference source

Divide this number by the mCi of Technetium Tc 99m. This result (µCi Mo99/mCi Tc 99m) can be converted to MBq Mo99/MBq Tc 99m by multiplying by 10^-3. The U.S. Pharmacopeia and the U.S. Nuclear Regulatory Commission or equivalent Agreement State regulations specify a limit of 0.00015MBq Molybdenum Mo99 per MBq of Technetium Tc 99m (0.15µCi Mo99/mCi Tc 99m) at the time of administration to each patient. If this limit is exceeded, the eluate should not be used. Discard the eluate and contact Lantheus Medical Imaging, Inc.

COLORIMETRIC ALUMINUM ION TEST PROCEDURE

Obtain an aluminum ion indicator kit and determine the aluminum ion concentration of the eluate per the manufacturer's instructions. The concentration must not exceed 10 micrograms per milliliter of eluate.

DISPOSAL: All components shipped with the TECHNELITE®, Technetium Tc 99m Generator should be monitored for contamination prior to disposing into routine trash systems. The Technetium Tc 99m should not be disposed of into routine trash systems. The generator should be disposed through a USNRC or Agreement State licensed disposal agency or by a method approved by the appropriate regulatory authority. Spent generators may be returned; complete return instructions are available on request.

This radioactive drug is approved for distribution to persons licensed pursuant to the Code of Massachusetts Regulations 105 CMR 120.100 for the uses listed in 105 CMR 120.547 or 120.552 or under equivalent regulations of the U.S. Nuclear Regulatory Commision, an Agreement State or a Licensing State.

Lantheus
Medical Imaging
331 Treble Cove Road
N. Billerica, MA 01862 USA
For Ordering Call Toll-Free: 800-299-3431 All other business: 800-362-2668
(In Massachusetts and International, call 978-667-9531)

Patent: http://www.lantheus.com/patents/index.html

Lantheus
Medical Imaging
Printed in U.S.A.
513160-0824
October 2024

PRINCIPAL DISPLAY PANEL - Generator Label - NDC 11994-090

Sterile, Non-Pyrogenic Diagnostic Agent for Intravenous Injection

TechneLite®
Technetium Tc 99m Generator
for the Production of Sodium Pertechnetate Tc 99m Injection

Rx only.

See Package Insert for dosing information.
DIN 02328550 AUSTR R 130301

Store at 20° to 25°C (68° to 77°F) [see USP Controlled
Room Temperature]. Eluate must be used within
12 hours of elution.

CAUTION: This generator should not be dismantled.

Manufacturer:
Lantheus
Medical Imaging®
N. Billerica, Massachusetts 01862 USA

Canadian License Holder:
Lantheus MI Canada, Inc.
Montréal, Canada H4M 2X6
Australian Sponsor:
Global Medical Solutions Australia Pty Ltd.

515128-1023

CAUTION:
RADIOACTIVE MATERIAL

PRINCIPAL DISPLAY PANEL - Generator Label - NDC 11994-091

Sterile, Non-Pyrogenic Diagnostic Agent for Intravenous Injection

TechneLite®
Technetium Tc 99m Generator
for the Production of Sodium Pertechnetate Tc 99m Injection

Rx only.

See Package Insert for dosing information.
DIN 02328550 AUSTR R 130301

Store at 20° to 25°C (68° to 77°F) [see USP Controlled
Room Temperature]. Eluate must be used within
12 hours of elution.

CAUTION: This generator should not be dismantled.

Manufacturer:
Lantheus
Medical Imaging®
N. Billerica, Massachusetts 01862 USA

Canadian License Holder:
Lantheus MI Canada, Inc.
Montréal, Canada H4M 2X6
Australian Sponsor:
Global Medical Solutions Australia Pty Ltd.

515128-1023

CAUTION:
RADIOACTIVE MATERIAL